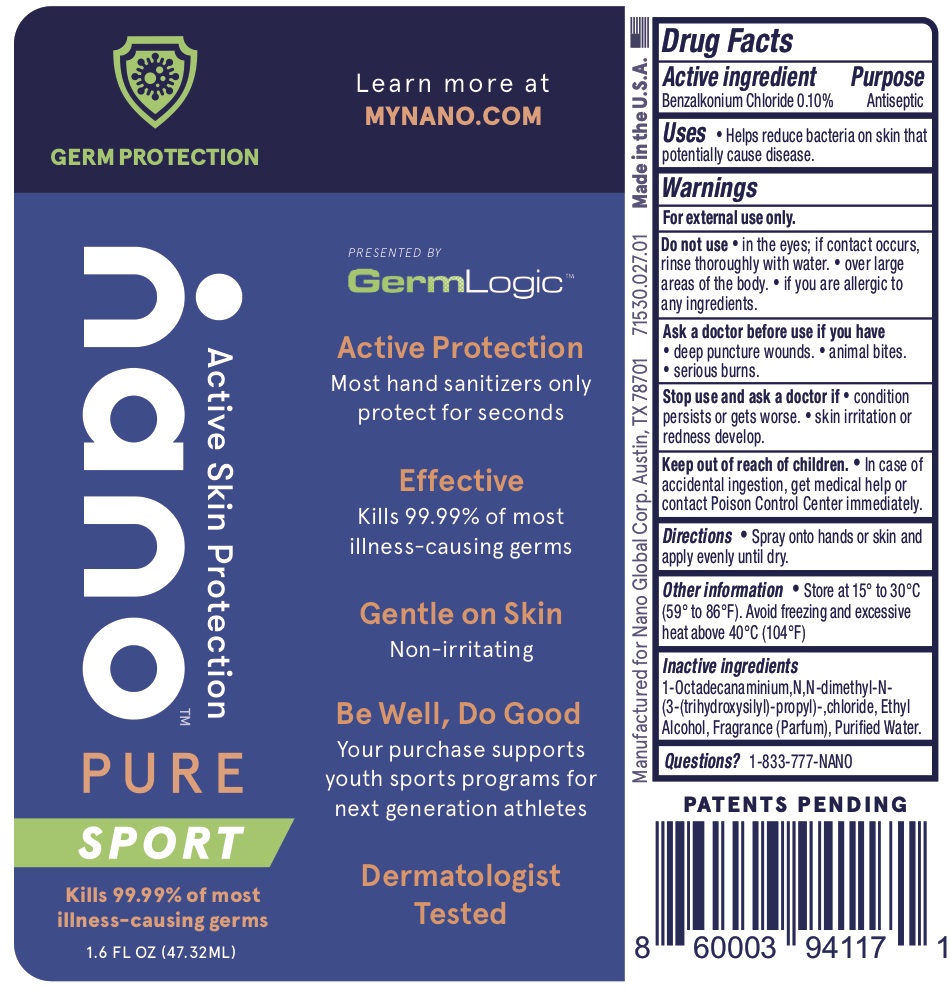 DRUG LABEL: Nano Pure Sport
NDC: 71530-027 | Form: LIQUID
Manufacturer: Nano Global
Category: otc | Type: HUMAN OTC DRUG LABEL
Date: 20200925

ACTIVE INGREDIENTS: BENZALKONIUM CHLORIDE 0.1 g/100 mL
INACTIVE INGREDIENTS: 1-OCTADECANAMINIUM, N,N-DIMETHYL-N-(3-(TRIHYDROXYSILYL)PROPYL) CHLORIDE; ALCOHOL; WATER

Nano Pure Sport

Active Ingredients

Benzalkonium Chloride 0.10%

Purpose

Antiseptic

Uses

• Helps reduce bacteria on skin that potentially cause disease.

Warnings

For external use only.

Do not use

• in the eyes; if contact occurs, rinse thoroughly with water.

• over large areas of the body.

• if you are allergic to any ingredients.

Ask a doctor before use if you have

• deep puncture wounds.

• animal bites.

• serious burns.

Stop use and ask a doctor if

• condition persists or gets worse.

• skin irritation or redness develop.

Keep out of reach of children.

• In case of accidental ingestion, get medical help or contact Poison Control Center immediately.

Directions

•Spray onto hands or skin and apply evenly until dry.

Other information

• Store at 15° to 30°C (59° to 86°F). Avoid freezing and excessive heat above 40°C (104°F)

Inactive Ingredients

1-Octadecanaminium,N,N-dimethyl-N(3-(trihydroxysilyl)-propyl)-chloride, Ethyl Alcohol, Fragrance (Parfum), Purified Water.

Questions?

1-833-777-NANO